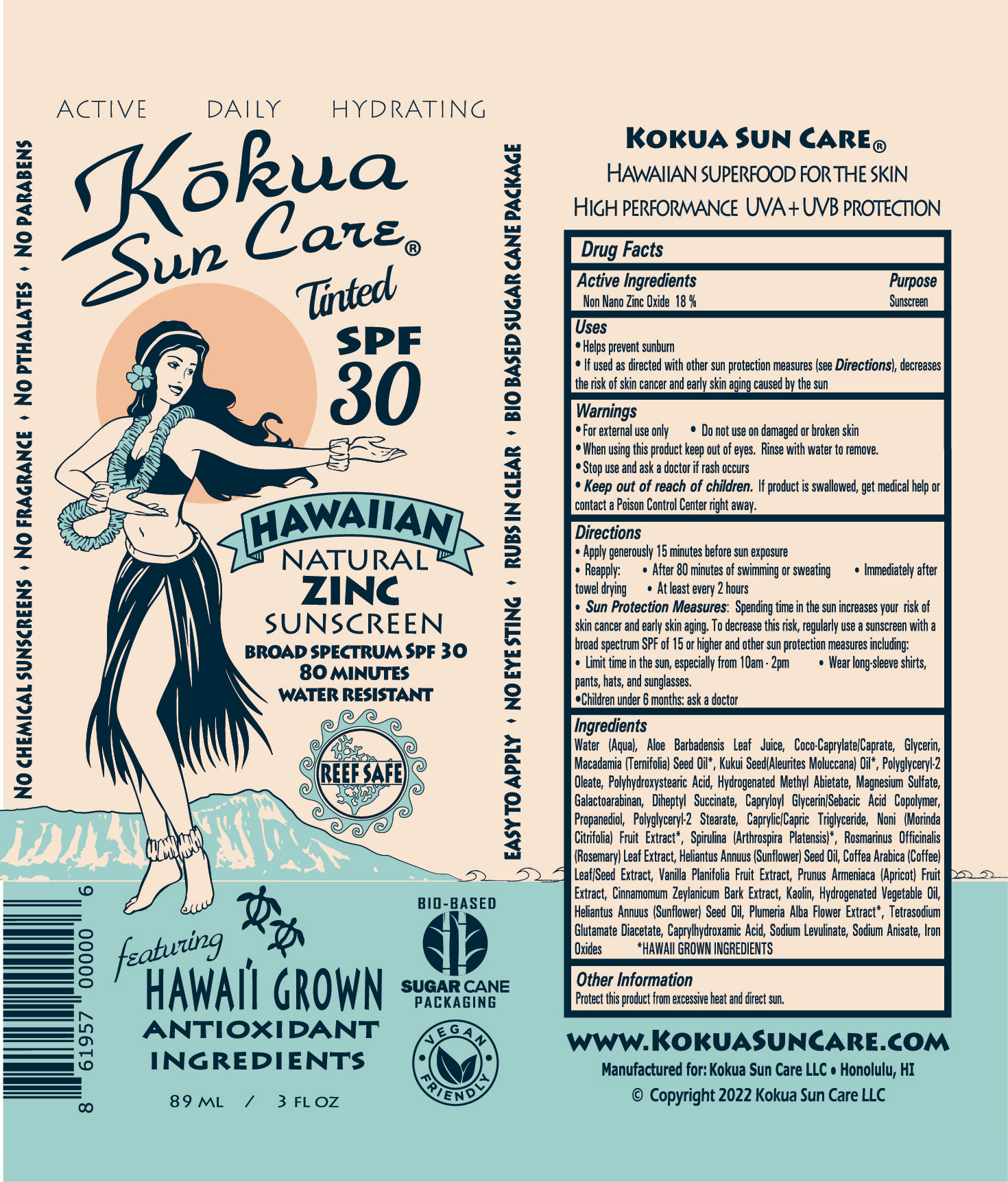 DRUG LABEL: Hawaiian Natural Zinc Sunscreen Broad Spectrum Tinted SPF 30
NDC: 72096-102 | Form: CREAM
Manufacturer: Kokua Sun Care
Category: otc | Type: HUMAN OTC DRUG LABEL
Date: 20251229

ACTIVE INGREDIENTS: ZINC OXIDE 18 g/100 mL
INACTIVE INGREDIENTS: TREHALOSE; MAGNESIUM SULFATE; NONI FRUIT; ARTHROSPIRA PLATENSIS; ROSEMARY; CAPRYLOYL GLYCERIN/SEBACIC ACID COPOLYMER (2000 MPA.S); FERROSOFERRIC OXIDE; FERRIC OXIDE RED; FERRIC OXIDE YELLOW; MEDIUM-CHAIN TRIGLYCERIDES; PLUMERIA ALBA FLOWER; COCO-CAPRYLATE/CAPRATE; MACADAMIA OIL; KAOLIN; WATER; POLYGLYCERYL-2 OLEATE; GALACTOARABINAN; DIHEPTYL SUCCINATE; PROPANEDIOL; GLYCERIN; ALOE VERA LEAF; TETRASODIUM GLUTAMATE DIACETATE; SUNFLOWER OIL; SODIUM LEVULINATE; SODIUM ANISATE; VANILLA BEAN; CAPRYLHYDROXAMIC ACID; POLYGLYCERYL-2 STEARATE; POLYHYDROXYSTEARIC ACID (2300 MW); HYDROGENATED METHYL ABIETATE; ALEURITES MOLUCCANUS SEED OIL; COCOS NUCIFERA (COCONUT) FRUIT

Kokua Hawaiian Natural Zinc Sunscreen Broad Spectrum Tinted SPF 30 (89 ml / 3 fl oz)

Active Ingredients

Non Nano Zinc Oxide 18%

Purpose

Sunscreen

Uses

- Helps prevent sunburn
- If used as directed with other sun protection measures (see Directions), decreases the risk of skin cancer and early skin aging

Keep out of reach of children.If product is swallowed, get medical help or contact a Poison Control Center right away.

Stop use and ask a doctor if rash occurs

Warnings

- for external use only
- Do not use on damaged skin
- When using this product keep out of eyes. Rinse with water to remove

Directions

- Apply generously 15 minutes before sun exposure
  - Reapply
    - After 80 minutes of swimming or sweating
    - Immediately after towel drying
    - At least every 2 hours
    - Sun Protection Measures:Spending time in the sun increases your risk of skin cancer and early skin aging. To decrease this risk, regularly use a sunscreen with a broad spectrum SPF of 15 or higher and other sun protection measures including:
    - Limit time in the sun, especially from 10am - 2pm
    - Wear long-sleeve shirts, pants, hats, and sunglasses
    - Children under 6 months: ask a doctor

INACTIVE INGREDIENT

Water (Aqua), Aloe Barbadensis Leaf Juice, Coco-caprylate/Caprate, Glycerin, Macademia (Ternifolia) Seed Oil, Kukui Seed(Aleurites Moluccana) Oil, Polyglyceryl-2 Oleate, Polyhydroxystearic Acid, Hydrogenated Methyl Abietate, Magnesium Sulfate, Galactoarabinan, Diheptyl Succinate, Capryloyl Glycerin/Sebacic Acid Copolymer, Propanediol, Polyglyceryl-2 Stearate, Caprylic/Capric Triglyceride, Noni (Morinda Citrifola) Fruit Extract, Spirulina (Arthrospira Platensis), Rosmarinus Officinalis (Rosemary) Leaf Extract, Helianthus Annuus (Sunflower) Seed Oil, Coffea Arabica (Coffee) Leaf/Seed Extract, Vanilla planifolia Fruit Extract, Prunus Armeniaca (Apricot) Fruit Extract, Cinnamomium Zeylanicum Bark Extract, Kaolin, Hydrogenated Vegetable Oil, Helianthus Annuus (Sunflower) Seed Oil, Plumeria Alba Flower Extract, Tetrasodium Glutamate Diacetate, Caprylhydroxamic Acid, Sodium Levulinate, Sodium Anisate, Iron oxides

PACKAGE LABEL

Kokua Sun Care

Tinted SPF 30

Hawaiian Natural Zinc Sunscreen Broad Spectrum SPF 30

80 Minutes

Water Resistant

89 ML/ 3 FL OZ